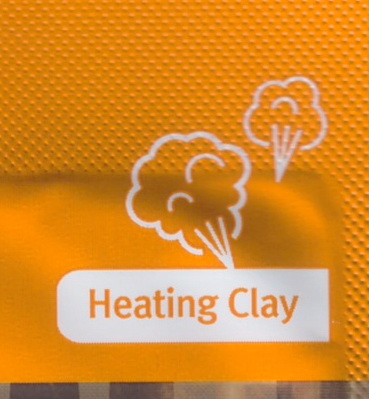 DRUG LABEL: OERBEUA HEATING PORE CRAY PACK
NDC: 71342-0028 | Form: LIQUID
Manufacturer: DR.GLODERM
Category: otc | Type: HUMAN OTC DRUG LABEL
Date: 20180110

ACTIVE INGREDIENTS: GLYCERIN 10.5 g/100 g
INACTIVE INGREDIENTS: BUTYLENE GLYCOL; TOCOPHEROL

Drug Facts

ACTIVE INGREDIENT

Glycerin

INACTIVE INGREDIENT

butylene glycol, tocopherol, etc

PURPOSE

Skin Protectant

keep out of reach of the children

INDICATIONS AND USAGE

1. after cleansing, apply the STEP 1 over dry face for feeling the warmth

2. after 5 minutes, rinse well with warm water as if massaging

WARNINGS

1. If the following symptoms occur after product use, stop using the product immediately and consult a dermatologist (continuous use can exacerbate the symptoms).
1) Occurrence of red spots, swelling, itchiness, and other skin irritation
2) If the symptoms above occur after the application area is exposed to direct sunlight
2. Do not use on open wounds, eczema, and other skin irritations
3. Precaution for Storage and Handling
1) Close the lid after use
2) Keep out of reach of infants and children
3) Do not to store in a place with high/low temperature and exposed to direct sunlight

DOSAGE AND ADMINISTRATION

for external use only